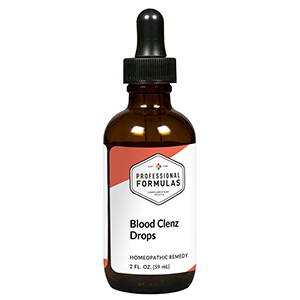 DRUG LABEL: Blood Clenz Drops
NDC: 63083-2012 | Form: LIQUID
Manufacturer: Professional Complementary Health Formulas
Category: homeopathic | Type: HUMAN OTC DRUG LABEL
Date: 20190815

ACTIVE INGREDIENTS: TRIFOLIUM PRATENSE FLOWER 3 [hp_X]/59 mL; SMILAX ORNATA ROOT 4 [hp_X]/59 mL; BERBERIS VULGARIS ROOT BARK 6 [hp_X]/59 mL; BEEF LIVER 6 [hp_X]/59 mL; BOS TAURUS LYMPH VESSEL 6 [hp_X]/59 mL; CHOLESTEROL 12 [hp_X]/59 mL; CALCIUM SULFIDE 12 [hp_X]/59 mL; BLACK WALNUT 12 [hp_X]/59 mL; HEMOGLOBIN 30 [hp_X]/59 mL
INACTIVE INGREDIENTS: ALCOHOL; WATER

C12

ACTIVE INGREDIENTS

Trifolium pratense 3X, 6X, 12X
Sarsaparilla 4X
Berberis vulgaris 6X
Liver 6X, 12X
Lymph 6X, 12X
Cholesterinum 12X
Hepar sulphuris calcareum 12X
Juglans nigra 12X, 20X
Hemoglobin 30X

QUESTIONS

Professional Formulas

PO Box 2034 Lake Oswego, OR 97035

INDICATIONS

For temporary relief of acne, pimples, dry or itching skin, occasional headaches, or fatigue.*

PURPOSE

*Claims based on traditional homeopathic practice, not accepted medical evidence. Not FDA evaluated.

WARNINGS

In case of overdose, get medical help or contact a poison control center right away.

Keep out of the reach of children.

PREGNANCY OR BREAST FEEDING

If pregnant or breastfeeding, ask a healthcare professional before use.

DIRECTIONS

Place drops under tongue 30 minutes before/after meals. Adults and children 12 years and over: Take 10 drops up to 3 times per day. Consult a physician for use in children under 12 years of age.

OTHER INFORMATION

Tamper resistant. If seal is broken, do not use. After opening, close container tightly and store at room temperature away from heat.

INACTIVE INGREDIENTS

20% ethanol, purified water.

LABEL

Est 1985

Professional Formulas

Complementary Health

Blood Clenz Drops

Homeopathic Remedy

2 FL. OZ. (59 mL)